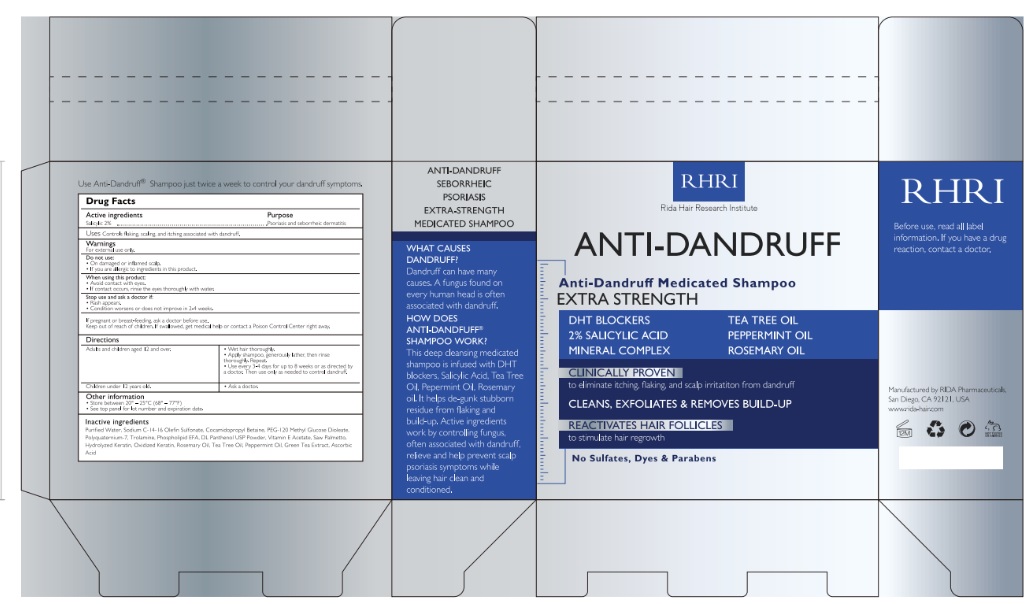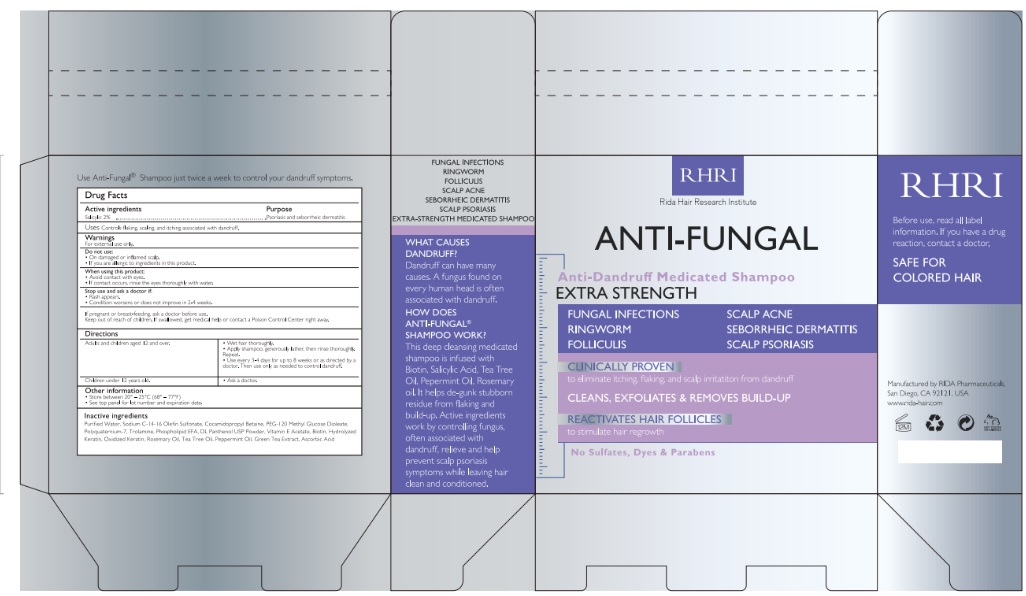 DRUG LABEL: Rida Hair Research Institute
NDC: 83004-001 | Form: LIQUID
Manufacturer: Rida LLC
Category: otc | Type: HUMAN OTC DRUG LABEL
Date: 20230316

ACTIVE INGREDIENTS: SALICYLIC ACID 3 g/100 mL
INACTIVE INGREDIENTS: WATER; SODIUM C14-16 OLEFIN SULFONATE; COCAMIDOPROPYL BETAINE; PEG-120 METHYL GLUCOSE DIOLEATE; POLYQUATERNIUM-7 (70/30 ACRYLAMIDE/DADMAC; 1600000 MW); TROLAMINE; PANTHENOL; .ALPHA.-TOCOPHEROL ACETATE; TEA TREE OIL; GREEN TEA LEAF; ASCORBIC ACID

Active Ingredient

Salicylic Acid 3%

Purpose

Psoriasis , dandruff and seborrheic dermatitis

Uses

Relieves and helps prevent recurrence of scalp irritation, flaking , itching, redness , scaling

Warnings

For external use only

Do not use

- On damaged or inflamed scalp
- if you are allergic to ingredients in this product

When using this product

- Avoid contact with eyes
- if contact occurs, rinse the eyes thoroughly with water

Stop use and ask a doctor if

- rash appears
- condition worsens or does not improve in 2-4 weeks.

If pregnant or breast-feeding, ask a doctor use.

Keep out of reach of children. if swallowed, get medical help or contact a Poison Control Center right away.

Directions

Adults and children aged 12 and over :

- wet hair thoroughly
- apply shampoo, generously lather, then rinse thoroughly. Repeate.
- Use every 3-4 days for up to 8 weeks or as direacted by a doctor. Then use only as needed to control dandruff

Cildren under 12 years old

- ask a doctor

Other Information

- store between 20° - 25°C (68° - 77°F)
- see bottom panel for lot number and expiration date

Inactive ingredients

Water, Sodium C14-16 Olefin Sulfonate, Cocamidopropyl Betaine, Peg-120 Methyl Glucose Dioleate, Polyquaternium-7 (70/30 Acrylamide/Dadmac; 1600000 Mw), Trolamine, Panthenol, .Alpha.-Tocopherol Acetate, Tea Tree Oil, Green Tea Leaf, Ascorbic Acid